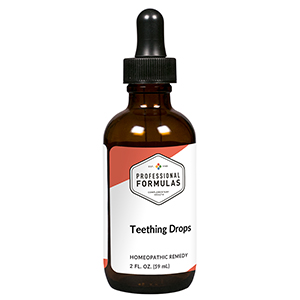 DRUG LABEL: Teething Drops
NDC: 63083-2120 | Form: LIQUID
Manufacturer: Professional Complementary Health Formulas
Category: homeopathic | Type: HUMAN OTC DRUG LABEL
Date: 20190815

ACTIVE INGREDIENTS: EUGENOL 3 [hp_X]/59 mL; ULMUS RUBRA BARK 3 [hp_X]/59 mL; ARTEMISIA ANNUA FLOWERING TOP 3 [hp_X]/59 mL; MENTHA X PIPERITA WHOLE 4 [hp_X]/59 mL; CLEMATIS RECTA FLOWERING TOP 6 [hp_X]/59 mL; CITRULLUS COLOCYNTHIS FRUIT PULP 6 [hp_X]/59 mL; COPPER 6 [hp_X]/59 mL; MYRRH 6 [hp_X]/59 mL; BRYONIA ALBA ROOT 12 [hp_X]/59 mL; OYSTER SHELL CALCIUM CARBONATE, CRUDE 12 [hp_X]/59 mL
INACTIVE INGREDIENTS: ALCOHOL; WATER

C120

ACTIVE INGREDIENTS

Eugenol 3X
Ulmus fulva 3X
Chamomilla 3X, 6X, 12X
Mentha piperita 4X
Clematis erecta 6X
Colocynthis 6X
Cuprum metallicum 6X
Myrrha 6X
Bryonia 12X, 30X
Calcarea carbonica 12X, 30X

QUESTIONS

Professional Formulas

PO Box 2034 Lake Oswego, OR 97035

INDICATIONS

For temporary relief of pain or irritability associated with teething.*

PURPOSE

*Claims based on traditional homeopathic practice, not accepted medical evidence. Not FDA evaluated.

WARNINGS

Consult a doctor if accompanied by fever and symptoms such as lethargy, lack of appetite, vomiting, or diarrhea. Keep out of the reach of children. In case of overdose, get medical help or contact a poison control center right away. If pregnant or breastfeeding, ask a healthcare professional before use.

Keep out of the reach of children.

PREGNANCY OR BREAST FEEDING

If pregnant or breastfeeding, ask a healthcare professional before use.

DIRECTIONS

Place drops under tongue 30 minutes before/after meals. Adults and children 12 years and over: Take 10 drops up to 3 times per day for up to 6 weeks. For immediate onset of symptoms, take 10 to 15 drops every 15 minutes up to 3 hours. For less severe symptoms, take 10-15 drops hourly up to 8 hours. Consult a physician for use in children under 12 years of age.

OTHER INFORMATION

Tamper resistant. If seal is broken, do not use. After opening, close container tightly and store at room temperature away from heat.

INACTIVE INGREDIENTS

10% ethanol, purified water, 8% vegetable glycerin (from soy).

LABEL

Est 1985

Professional Formulas

Complementary Health

Teething Drops

Homeopathic Remedy

2 FL. OZ. (59 mL)